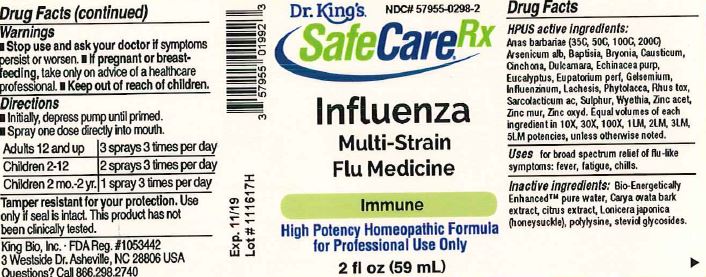 DRUG LABEL: Influenza Multi-Strain Flu Medicine
NDC: 57955-0298 | Form: LIQUID
Manufacturer: King Bio Inc.
Category: homeopathic | Type: HUMAN OTC DRUG LABEL
Date: 20180122

ACTIVE INGREDIENTS: CAIRINA MOSCHATA HEART/LIVER AUTOLYSATE 35 [hp_C]/59 mL; ARSENIC TRIOXIDE 10 [hp_X]/59 mL; BAPTISIA TINCTORIA ROOT 10 [hp_X]/59 mL; BRYONIA ALBA ROOT 10 [hp_X]/59 mL; CAUSTICUM 10 [hp_X]/59 mL; CINCHONA OFFICINALIS BARK 10 [hp_X]/59 mL; SOLANUM DULCAMARA TOP 10 [hp_X]/59 mL; ECHINACEA PURPUREA 10 [hp_X]/59 mL; EUCALYPTUS GLOBULUS LEAF 10 [hp_X]/59 mL; EUPATORIUM PERFOLIATUM FLOWERING TOP 10 [hp_X]/59 mL; GELSEMIUM SEMPERVIRENS ROOT 10 [hp_X]/59 mL; INFLUENZA A VIRUS 10 [hp_X]/59 mL; LACHESIS MUTA VENOM 10 [hp_X]/59 mL; PHYTOLACCA AMERICANA ROOT 10 [hp_X]/59 mL; TOXICODENDRON PUBESCENS LEAF 10 [hp_X]/59 mL; LACTIC ACID, L- 10 [hp_X]/59 mL; SULFUR 10 [hp_X]/59 mL; WYETHIA HELENIOIDES ROOT 10 [hp_X]/59 mL; ZINC ACETATE ANHYDROUS 10 [hp_X]/59 mL; ZINC OXIDE 10 [hp_X]/59 mL; ZINC CHLORIDE 10 [hp_X]/59 mL
INACTIVE INGREDIENTS: WATER; CARYA OVATA BARK; CITRUS BIOFLAVONOIDS; LONICERA JAPONICA FLOWER; POLYEPSILON-LYSINE (4000 MW); REBAUDIOSIDE A

Influenza Multi-Strain Flu Medicine

HPUS Active Ingredients

Anas barbariae (35C, 50C, 100C, 200C), Arsenicum alb, Baptisia, Bryonia, Causticum, Cinchona, Dulcamara, Echinacea purp, Eucalyptus, Eupatorium perf, Gelsemium, Influenzinum, Lachesis, Phytolacca, Rhus tox, Sarcolacticum ac, Sulphur, Wyethia, Zincum acet, Zincum mur, Zincum oxyd.

Equal volumes of each ingredient in 10X, 30X, 100X, 1LM, 2LM, 3LM, 5LM potensiec, unless otherwise noted.

Inactive Ingredients

Bio-Energetically EnhancedTM pure water, Carya ovata bark extract, citrus extract, Lonicera japonica (honeysuckle), polylysine, steviol glycosides.

Directions

- Initially, depress pump until primed.
- Spray one dose directly into mouth.
- Adults 12 and up: 3 sprays 3 times per day.
- Children 2-12: 2 sprays 3 times per day.
- Children 2mo-2yr.: 1 spray 3 times per day.

Warnings

- Stop use and ask a doctor if symptoms persist or worsen.
- If pregnant or breast-feeding, take only on advice of a healthcare professional.

- Keep out of reach of children.

Other Safety Information

Tamper resistant for your protection. Use only if safety seal is intact. This product has not been clinically tesed.

PURPOSE

Uses for broad spectrum relief of flu-like symptoms: fever, fatigue, chills.

Uses

Uses for broad spectrum relief of flu-like symptoms: fever, fatigue, chills.